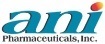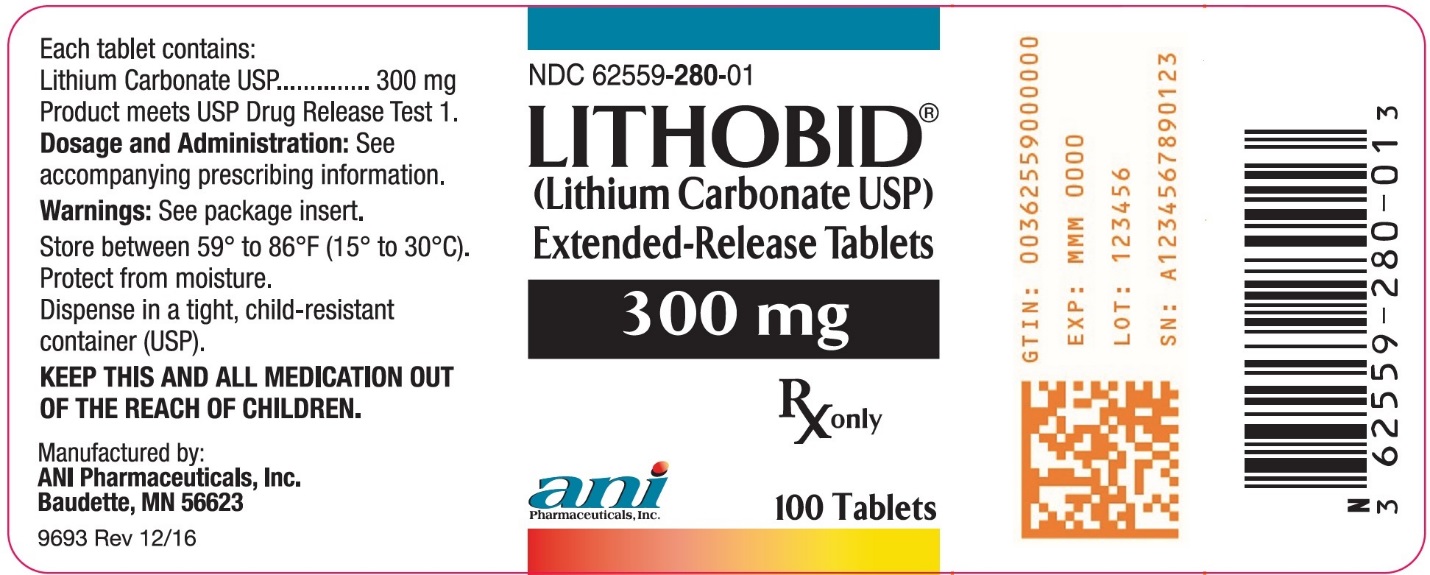 DRUG LABEL: LITHOBID
NDC: 62559-280 | Form: TABLET, FILM COATED, EXTENDED RELEASE
Manufacturer: ANI Pharmaceuticals, Inc.
Category: prescription | Type: HUMAN PRESCRIPTION DRUG LABEL
Date: 20221028

ACTIVE INGREDIENTS: LITHIUM CARBONATE 300 mg/1 1
INACTIVE INGREDIENTS: CALCIUM STEARATE; CARNAUBA WAX; FD&C Blue No. 2; FD&C Red No. 40; FD&C Yellow No. 6; HYDROXYPROPYL CELLULOSE, UNSPECIFIED; HYPROMELLOSE 2910 (50 MPA.S); POVIDONE K30; PROPYLENE GLYCOL; SODIUM CHLORIDE; SODIUM LAURYL SULFATE; SODIUM STARCH GLYCOLATE TYPE A POTATO; SORBITOL; TITANIUM DIOXIDE

LITHOBID® (Lithium Carbonate USP)
Extended-Release Tablets 300 mg

Rx only

WARNING

Lithium toxicity is closely related to serum lithium levels, and can occur at doses close to therapeutic levels. Facilities for prompt and accurate serum lithium determinations should be available before initiating therapy (see DOSAGE AND ADMINISTRATION).

DESCRIPTION

LITHOBID® tablets contain lithium carbonate, a white odorless alkaline powder with molecular formula Li2CO3 and molecular weight 73.89. Lithium is an element of the alkali-metal group with atomic number 3, atomic weight 6.94, and an emission line at 671 nm on the flame photometer.

Each peach-colored, film-coated, extended-release tablet contains 300 mg of lithium carbonate. This slowly dissolving film-coated tablet is designed to give lower serum lithium peak concentrations than obtained with conventional oral lithium dosage forms. Inactive ingredients consist of calcium stearate, carnauba wax, cellulose compounds, FD&C Blue No. 2 Aluminum Lake, FD&C Red No. 40 Aluminum Lake, FD&C Yellow No. 6 Aluminum Lake, povidone, propylene glycol, sodium chloride, sodium lauryl sulfate, sodium starch glycolate, sorbitol, and titanium dioxide. Product meets USP Drug Release Test 1.

ACTIONS

Preclinical studies have shown that lithium alters sodium transport in nerve and muscle cells and effects a shift toward intraneuronal metabolism of catecholamines, but the specific biochemical mechanism of lithium action in mania is unknown.

INDICATIONS

LITHOBID® (lithium carbonate) is indicated in the treatment of manic episodes of Bipolar Disorder. Bipolar Disorder, Manic (DSM-IV) is equivalent to Manic Depressive illness, Manic, in the older DSM-II terminology. LITHOBID® is also indicated as a maintenance treatment for individuals with a diagnosis of Bipolar Disorder. Maintenance therapy reduces the frequency of manic episodes and diminishes the intensity of those episodes which may occur.

Typical symptoms of mania include pressure of speech, motor hyperactivity, reduced need for sleep, flight of ideas, grandiosity, elation, poor judgment, aggressiveness, and possibly hostility. When given to a patient experiencing a manic episode, lithium may produce a normalization of symptomatology within 1 to 3 weeks.

WARNINGS

Lithium Toxicity

The toxic concentrations for lithium (≥1.5 mEq/L) are close to the therapeutic range (0.8 to 1.2 mEq/L). Some patients abnormally sensitive to lithium may exhibit toxic signs at serum concentrations that are considered within the therapeutic range (see BOXED WARNING and DOSAGE AND ADMINISTRATION). Lithium may take up to 24 hours to distribute into brain tissue, so occurrence of acute toxicity symptoms may be delayed.

Neurological signs of lithium toxicity range from mild neurological adverse reactions such as fine tremor, lightheadedness, lack of coordination, and weakness; to moderate manifestations like giddiness, apathy, drowsiness, hyperreflexia, muscle twitching, ataxia, blurred vision, tinnitus, and slurred speech; and severe manifestations such as clonus, confusion, seizure, coma, and death. In rare cases, neurological sequelae may persist despite discontinuing lithium treatment and may be associated with cerebellar atrophy. Cardiac manifestations involve electrocardiographic changes, such as prolonged QT interval, ST and T-wave changes and myocarditis. Renal manifestations include urine concentrating defect, nephrogenic diabetes insipidus, and renal failure. Respiratory manifestations include dyspnea, aspiration pneumonia, and respiratory failure. Gastrointestinal manifestations include nausea, vomiting, diarrhea, and bloating. No specific antidote for lithium poisoning is known (see OVERDOSAGE).

The risk of lithium toxicity is increased by:

- Recent onset of concurrent febrile illness
- Concomitant administration of drugs which increase lithium serum concentrations by pharmacokinetic interactions or drugs affecting kidney function (see PRECAUTIONS-Drug Interactions)
- Acute ingestion
- Impaired renal function
- Volume depletion or dehydration
- Significant cardiovascular disease
- Changes in electrolyte concentrations (especially sodium and potassium)

Monitor for signs and symptoms of lithium toxicity. If symptoms occur, decrease dosage or discontinue lithium treatment.

Unmasking of Brugada Syndrome

There have been postmarketing reports of a possible association between treatment with lithium and the unmasking of Brugada Syndrome. Brugada Syndrome is a disorder characterized by abnormal electrocardiographic (ECG) findings and a risk of sudden death. Lithium should generally be avoided in patients with Brugada Syndrome or those suspected of having Brugada Syndrome. Consultation with a cardiologist is recommended if: (1) treatment with lithium is under consideration for patients suspected of having Brugada Syndrome or patients who have risk factors for Brugada Syndrome, e.g., unexplained syncope, a family history of Brugada Syndrome, or a family history of sudden unexplained death before the age of 45 years, (2) patients who develop unexplained syncope or palpitations after starting lithium therapy.

Psuedotumor Cerebri

Cases of pseudotumor cerebri (increased intracranial pressure and papilledema) have been reported with lithium use. If undetected, this condition may result in enlargement of the blind spot, constriction of visual fields, and eventual blindness due to optic atrophy. Lithium should be discontinued, if clinically possible, if this syndrome occurs.

Renal Effects

Chronic lithium therapy may be associated with diminution of renal concentrating ability, occasionally presenting as nephrogenic diabetes insipidus, with polyuria and polydipsia. Such patients should be carefully managed to avoid dehydration with resulting lithium retention and toxicity. This condition is usually reversible when lithium is discontinued.

Post marketing cases consistent with nephrotic syndrome have been reported with the use of lithium. Biopsy findings in patients with nephrotic syndrome include minimal change disease and focal segmental glomerulosclerosis. Discontinuation of lithium in patients with nephrotic syndrome has resulted in remission of nephrotic syndrome.

Morphologic changes with glomerular and interstitial fibrosis and nephron atrophy have been reported in patients on chronic lithium therapy. Morphologic changes have also been seen in manic-depressive patients never exposed to lithium. The relationship between renal function and morphologic changes and their association with lithium therapy have not been established.

Kidney function should be assessed prior to and during lithium therapy. Routine urinalysis and other tests may be used to evaluate tubular function (e.g., urine specific gravity or osmolality following a period of water deprivation, or 24-hour urine volume) and glomerular function (e.g., serum creatinine, creatinine clearance, or proteinuria). During lithium therapy, progressive or sudden changes in renal function, even within the normal range, indicate the need for re-evaluation of treatment.

Encephalopathic Syndrome

An encephalopathic syndrome (characterized by weakness, lethargy, fever, tremulousness and confusion, extrapyramidal symptoms, leukocytosis, elevated serum enzymes, BUN, and FBS) has occurred in a few patients treated with lithium plus a neuroleptic, most notably haloperidol. In some instances, the syndrome was followed by irreversible brain damage. Because of possible causal relationship between these events and the concomitant administration of lithium and neuroleptic drugs, patients receiving such combined therapy or patients with organic brain syndrome or other CNS impairment should be monitored closely for early evidence of neurologic toxicity and treatment discontinued promptly if such signs appear. This encephalopathic syndrome may be similar to or the same as Neuroleptic Malignant Syndrome (NMS).

Serotonin Syndrome

Lithium can precipitate serotonin syndrome, a potentially life-threatening condition. The risk is increased with concomitant use of other serotonergic drugs (including selective serotonin reuptake inhibitors, serotonin and norepinephrine reuptake inhibitors, triptans, tricyclic antidepressants, fentanyl, tramadol, tryptophan, buspirone, and St. John’s Wort) and with drugs that impair metabolism of serotonin, i.e., MAOIs (see PRECAUTIONS).

Serotonin syndrome signs and symptoms may include mental status changes (e.g., agitation, hallucinations, delirium, and coma), autonomic instability (e.g., tachycardia, labile blood pressure, dizziness, diaphoresis, flushing, hyperthermia), neuromuscular symptoms (e.g., tremor, rigidity, myoclonus, hyperreflexia, incoordination), seizures, and gastrointestinal symptoms (e.g., nausea, vomiting, diarrhea).

Monitor all patients taking lithium for the emergence of serotonin syndrome. Discontinue treatment with lithium and any concomitant serotonergic agents immediately if the above symptoms occur and initiate supportive symptomatic treatment. If concomitant use of lithium with other serotonergic drugs is clinically warranted, inform patients of the increased risk for serotonin syndrome and monitor for symptoms.

Concomitant Use with Neuromuscular Blocking Agents

Lithium may prolong the effects of neuromuscular blocking agents. Therefore, neuromuscular blocking agents should be given with caution to patients receiving lithium.

Usage in Pregnancy

Adverse effects on nidation in rats, embryo viability in mice, and metabolism in vitro of rat testis and human spermatozoa have been attributed to lithium, as have teratogenicity in submammalian species and cleft palate in mice.

In humans, lithium may cause fetal harm when administered to a pregnant woman. Data from lithium birth registries suggest an increase in cardiac and other anomalies, especially Ebstein's anomaly. If this drug is used in women of childbearing potential, or during pregnancy, or if a patient becomes pregnant while taking this drug, the patient should be apprised by their physician of the potential hazard to the fetus.

Usage in Nursing Mothers

Lithium is excreted in human milk. Nursing should not be undertaken during lithium therapy except in rare and unusual circumstances where, in the view of the physician, the potential benefits to the mother outweigh possible hazard to the infant or neonate. Signs and symptoms of lithium toxicity such as hypertonia, hypothermia, cyanosis, and ECG changes have been reported in some infants and neonates.

Pediatric Use

Safety and effectiveness in pediatric patients under 12 years of age have not been determined; its use in these patients is not recommended.

There has been a report of transient syndrome of acute dystonia and hyperreflexia occurring in a 15 kg pediatric patient who ingested 300 mg of lithium carbonate.

PRECAUTIONS

The ability to tolerate lithium is greater during the acute manic phase and decreases when manic symptoms subside (see DOSAGE AND ADMINISTRATION).

The distribution space of lithium approximates that of total body water. Lithium is primarily excreted in urine with insignificant excretion in feces. Renal excretion of lithium is proportional to its plasma concentration. The elimination half-life of lithium is approximately 24 hours. Lithium decreases sodium reabsorption by the renal tubules which could lead to sodium depletion. Therefore, it is essential for the patient to maintain a normal diet, including salt, and an adequate fluid intake (2500 to 3500 mL) at least during the initial stabilization period. Decreased tolerance to lithium has been reported to ensue from protracted sweating or diarrhea and, if such occur, supplemental fluid and salt should be administered under careful medical supervision and lithium intake reduced or suspended until the condition is resolved.

In addition to sweating and diarrhea, concomitant infection with elevated temperatures may also necessitate a temporary reduction or cessation of medication.

Previously existing thyroid disorders do not necessarily constitute a contraindication to lithium treatment. Where hypothyroidism preexists, careful monitoring of thyroid function during lithium stabilization and maintenance allows for correction of changing thyroid parameters and/or adjustment of lithium doses, if any. If hypothyroidism occurs during lithium stabilization and maintenance, supplemental thyroid treatment may be used.

Drug Interactions

Diuretic-, ACE-, and ARB-induced sodium loss may increase serum lithium concentrations. Start with lower doses of lithium or reduce dosage, while frequently monitoring serum lithium concentrations and signs of lithium toxicity. See WARNINGS for additional caution information.

Concomitant administration of lithium with serotonergic drugs can precipitate serotonin syndrome. Monitor patients for signs and symptoms of serotonin syndrome, particularly during lithium initiation. If serotonin syndrome occurs, consider discontinuation of lithium and/or concomitant serotonergic drugs. Examples of serotonergic drugs include selective serotonin reuptake inhibitors (SSRI), serotonin and norepinephrine reuptake inhibitors (SNRI), and monoamine oxidase inhibitors (MAOI).

Concomitant administration of methyldopa, phenytoin, or carbamazepine with lithium may increase the risk of adverse reactions with these drugs.

The following drugs can lower serum lithium concentrations by increasing urinary lithium excretion: acetazolamide, urea, xanthine preparations, and alkalinizing agents such as sodium bicarbonate.

Concomitant extended use of iodide preparations, especially potassium iodide, with lithium may produce hypothyroidism.

Concurrent use of calcium channel blocking agents with lithium may increase the risk of neurotoxicity in the form of ataxia, tremors, nausea, vomiting, diarrhea, and/or tinnitus.

Concurrent use of metronidazole with lithium may provoke lithium toxicity due to reduced renal clearance. Patients receiving such combined therapy should be monitored closely.

Concurrent use of fluoxetine with lithium has resulted in both increased and decreased serum lithium concentrations. Patients receiving such combined therapy should be monitored closely.

Nonsteroidal anti-inflammatory drugs (NSAIDs): Lithium levels should be closely monitored when patients initiate or discontinue NSAID use. In some cases, lithium toxicity has resulted from interactions between a NSAID and lithium. Indomethacin and piroxicam have been reported to increase significantly steady-state plasma lithium concentrations. There is also evidence that other nonsteroidal anti-inflammatory agents, including the selective cyclooxygenase-2 (COX-2) inhibitors, have the same effect. In a study conducted in healthy subjects, mean steady-state lithium plasma levels increased approximately 17% in subjects receiving lithium 450 mg BID with celecoxib 200 mg BID as compared to subjects receiving lithium alone.

Concomitant use of lithium with a Sodium-Glucose Cotransporter 2 (SGLT2) inhibitor may decrease serum lithium concentrations. Monitor serum lithium concentration more frequently during SGLT2 inhibitor initiation and dosage changes.

Lithium may impair mental and/or physical abilities. Patients should be cautioned about activities requiring alertness (e.g., operating vehicles or machinery).

Usage in Pregnancy

See WARNINGS.

Usage in Nursing Mothers

Because of the potential for serious adverse reactions in nursing infants and neonates from lithium, a decision should be made whether to discontinue nursing or to discontinue the drug, taking into account the importance of the drug to the mother (see WARNINGS).

Pediatric Use

Safety and effectiveness in pediatric patients below the age of 12 have not been established (see WARNINGS).

Geriatric Use

Clinical studies of LITHOBID® tablets did not include sufficient numbers of subjects aged 65 and over to determine whether they respond differently from younger subjects. Other reported clinical experience has not identified differences in responses between the elderly and younger patients. In general, dose selection for an elderly patient should be cautious, usually starting at the low end of the dosing range, reflecting the greater frequency of decreased hepatic, renal, or cardiac function, and of concomitant disease or other therapy.

This drug is known to be substantially excreted by the kidney, and the risk of toxic reactions to this drug may be greater in patients with impaired renal function. Because elderly patients are more likely to have decreased renal function, care should be taken in dose selection, and it may be useful to monitor renal function.

ADVERSE REACTIONS

The occurrence and severity of adverse reactions are generally directly related to serum lithium concentrations and to individual patient sensitivity to lithium. They generally occur more frequently and with greater severity at higher concentrations.

Adverse reactions may be encountered at serum lithium concentrations below 1.5 mEq/L. Mild to moderate adverse reactions may occur at concentrations from 1.5 to 2.5 mEq/L, and moderate to severe reactions may be seen at concentrations from 2.0 mEq/L and above.

Fine hand tremor, polyuria, and mild thirst may occur during initial therapy for the acute manic phase and may persist throughout treatment. Transient and mild nausea and general discomfort may also appear during the first few days of lithium administration.

These side effects usually subside with continued treatment or with a temporary reduction or cessation of dosage. If persistent, a cessation of lithium therapy may be required. Diarrhea, vomiting, drowsiness, muscular weakness, and lack of coordination may be early signs of lithium intoxication, and can occur at lithium concentrations below 2.0 mEq/L. At higher concentrations, giddiness, ataxia, blurred vision, tinnitus, and a large output of dilute urine may be seen. Serum lithium concentrations above 3.0 mEq/L may produce a complex clinical picture involving multiple organs and organ systems. Serum lithium concentrations should not be permitted to exceed 2.0 mEq/L during the acute treatment phase.

The following reactions have been reported and appear to be related to serum lithium concentrations, including concentrations within the therapeutic range:

Central Nervous System: tremor, muscle hyperirritability (fasciculations, twitching, clonic movements of whole limbs), hypertonicity, ataxia, choreoathetotic movements, hyperactive deep tendon reflex, extrapyramidal symptoms including acute dystonia, cogwheel rigidity, blackout spells, epileptiform seizures, slurred speech, dizziness, vertigo, downbeat nystagmus, incontinence of urine or feces, somnolence, psychomotor retardation, restlessness, confusion, stupor, coma, tongue movements, tics, tinnitus, hallucinations, poor memory, slowed intellectual functioning, startled response, worsening of organic brain syndromes. Cardiovascular: cardiac arrhythmia, hypotension, peripheral circulatory collapse, bradycardia, sinus node dysfunction with severe bradycardia (which may result in syncope), Unmasking of Brugada Syndrome (See WARNINGS and PATIENT COUNSELING INFORMATION). Gastrointestinal: anorexia, nausea, vomiting, diarrhea, gastritis, salivary gland swelling, abdominal pain, excessive salivation, flatulence, indigestion. Genitourinary: glycosuria, decreased creatinine clearance, albuminuria, oliguria, and symptoms of nephrogenic diabetes insipidus including polyuria, thirst and polydipsia. Dermatologic: drying and thinning of hair, alopecia, anesthesia of skin, acne, chronic folliculitis, xerosis cutis, psoriasis or its exacerbation, generalized pruritus with or without rash, cutaneous ulcers, angioedema, drug reaction with eosinophilia and systemic symptoms (DRESS). Autonomic Nervous System: blurred vision, dry mouth, impotence/sexual dysfunction. Thyroid Abnormalities: euthyroid goiter and/or hypothyroidism (including myxedema) accompanied by lower T3 and T4. ^131Iodine uptake may be elevated (see PRECAUTIONS). Paradoxically, rare cases of hyperthyroidism have been reported. EEG Changes: diffuse slowing, widening of frequency spectrum, potentiation and disorganization of background rhythm. EKG Changes: reversible flattening, isoelectricity or inversion of T-waves. Miscellaneous: fatigue, lethargy, transient scotomata, exophthalmos, dehydration, weight loss, leucocytosis, headache, transient hyperglycemia, hypercalcemia, hyperparathyroidism, albuminuria, excessive weight gain, edematous swelling of ankles or wrists, metallic taste, dysgeusia/taste distortion, salty taste, thirst, swollen lips, tightness in chest, swollen and/or painful joints, fever, polyarthralgia, and dental caries.

Some reports of nephrogenic diabetes insipidus, hyperparathyroidism, and hypothyroidism which persist after lithium discontinuation have been received.

A few reports have been received of the development of painful discoloration of fingers and toes and coldness of the extremities within one day of starting lithium treatment. The mechanism through which these symptoms (resembling Raynaud's Syndrome) developed is not known. Recovery followed discontinuance.

DOSAGE AND ADMINISTRATION

Acute Mania

Optimal patient response can usually be established with 1800 mg/day in the following dosages:

ACUTE MANIA
 | Morning | Afternoon | Nighttime
LITHOBID® Extended-Release Tablets^1 | 3 tabs (900 mg) |  | 3 tabs (900 mg)
^1Can also be administered on 600 mg TID recommended dosing interval.

Such doses will normally produce an effective serum lithium concentration ranging between 1.0 and 1.5 mEq/L. Dosage must be individualized according to serum concentrations and clinical response. Regular monitoring of the patient's clinical state and of serum lithium concentrations is necessary. Serum concentrations should be determined twice per week during the acute phase, and until the serum concentrations and clinical condition of the patient have been stabilized.

Long-Term Control

Desirable serum lithium concentrations are 0.6 to 1.2 mEq/L which can usually be achieved with 900 to 1200 mg/day. Dosage will vary from one individual to another, but generally the following dosages will maintain this concentration:

LONG-TERM CONTROL

Morning

Afternoon

Nighttime

LITHOBID®

Extended-Release Tablets^1

2 tabs

(600 mg)

2 tabs

(600 mg)

^1Can be administered on TID recommended dosing interval up to 1200 mg/day.

Serum lithium concentrations in uncomplicated cases receiving maintenance therapy during remission should be monitored at least every two months. Patients abnormally sensitive to lithium may exhibit toxic signs at serum concentrations of 1.0 to 1.5 mEq/L. Geriatric patients often respond to reduced dosage, and may exhibit signs of toxicity at serum concentrations ordinarily tolerated by other patients. In general, dose selection for an elderly patient should be cautious, usually starting at the low end of the dosing range, reflecting the greater frequency of decreased hepatic, renal, or cardiac function, and of concomitant disease or other drug therapy.

Important Considerations

- Blood samples for serum lithium determinations should be drawn immediately prior to the next dose when lithium concentrations are relatively stable (i.e., 8 to 12 hours after previous dose). Total reliance must not be placed on serum concentrations alone. Accurate patient evaluation requires both clinical and laboratory analysis.
- LITHOBID® Extended-Release Tablets must be swallowed whole and never chewed or crushed.

OVERDOSAGE

The toxic concentrations for lithium (≥ 1.5 mEq/L) are close to the therapeutic concentrations. It is therefore important that patients and their families be cautioned to watch for early toxic symptoms and to discontinue the drug and inform the physician should they occur (see WARNINGS: Lithium Toxicity).

Treatment

No specific antidote for lithium poisoning is known. Treatment is supportive. Early symptoms of lithium toxicity can usually be treated by reduction or cessation of dosage of the drug and resumption of the treatment at a lower dose after 24 to 48 hours. In severe cases of lithium poisoning, the first and foremost goal of treatment consists of elimination of this ion from the patient.

Treatment is essentially the same as that used in barbiturate poisoning: 1) gastric lavage, 2) correction of fluid and electrolyte imbalance and, 3) regulation of kidney functioning. Urea, mannitol, and aminophylline all produce significant increases in lithium excretion. Hemodialysis is an effective and rapid means of removing the ion from the severely toxic patient. However, patient recovery may be slow.

Infection prophylaxis, regular chest X-rays, and preservation of adequate respiration are essential.

PATIENT COUNSELING INFORMATION

Information for Patients: A condition known as Brugada Syndrome may pre-exist and be unmasked by lithium therapy. Brugada Syndrome is a heart disorder characterized by abnormal electrocardiographic (ECG) findings and risk of sudden death. Patients should be advised to seek immediate emergency assistance if they experience fainting, light-headedness, abnormal heart beats, or shortness of breath because they may have a potentially life-threatening heart disorder known as Brugada Syndrome.

HOW SUPPLIED

LITHOBID® (Lithium Carbonate USP) Extended-Release Tablets, 300 mg, peach-colored imprinted “LITHOBID 300”
NDC 62559-280-01 Bottle of 100

Storage Conditions

Store between 59° to 86°F (15° to 30°C). Protect from moisture. Dispense in tight, child-resistant container (USP).

Manufactured By:
ANI Pharmaceuticals, Inc.
Baudette, MN 56623
9694 Rev 10/22

Package/Label Display Panel

LITHOBID® (Lithium Carbonate USP) Extended-Release Tablets, 300 mg
NDC 62559-280-01
Rx only
100 Tablets